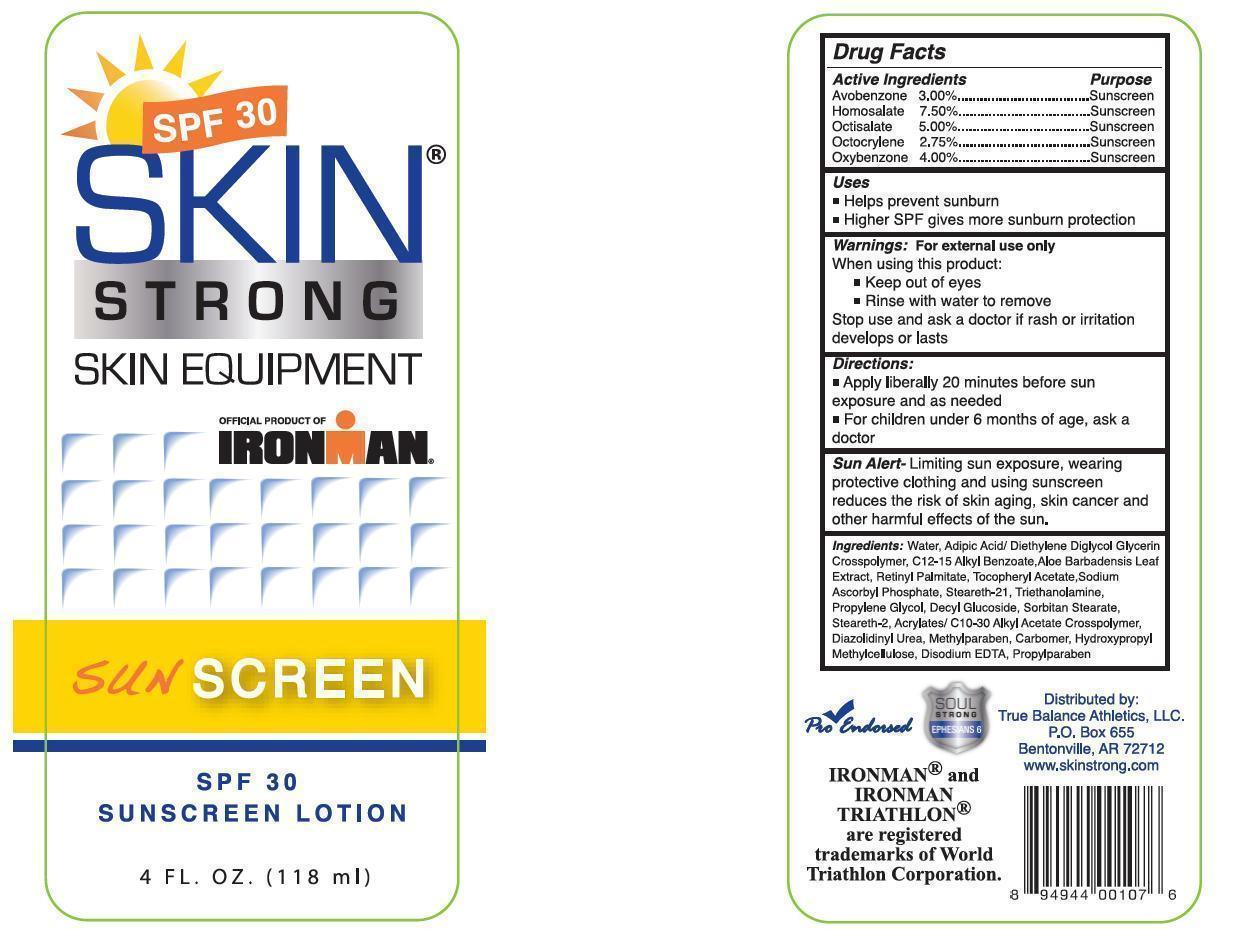 DRUG LABEL: SKIN STRONG - SKIN EQUIPMENT
NDC: 51401-030 | Form: LOTION
Manufacturer: True Balance Athletics LLC 
Category: otc | Type: HUMAN OTC DRUG LABEL
Date: 20121219

ACTIVE INGREDIENTS: AVOBENZONE 30 mg/1 mL; HOMOSALATE 75 mg/1 mL; OCTISALATE 50 mg/1 mL; OCTOCRYLENE 27.5 mg/1 mL; OXYBENZONE 40 mg/1 mL
INACTIVE INGREDIENTS: WATER; ALKYL (C12-15) BENZOATE; ALOE VERA LEAF; VITAMIN A PALMITATE; .ALPHA.-TOCOPHEROL ACETATE; SODIUM ASCORBYL PHOSPHATE; STEARETH-21

SKIN STRONG SKIN EQUIPMENT - SPF 30 SUNSCREEN LOTION - DRUG FACTS LABEL

ACTIVE INGREDIENTS

AVOBENZONE 3.00%, HOMOSALATE 7.5%, OCTISALATE 5.00%, OCTOCRYLENE 2.75%, OXYBENZONE 4.00%

PURPOSE

SUNSCREEN

USES

- HELPS PREVENT SUNBURN
- HIGHER SPF GIVES MORE SUNBURN PROTECTION

WARNINGS:

FOR EXTERNAL USE ONLY

WHEN USING THIS PRODUCT:

- KEEP OUT OF THE EYES
- RINSE WITH WATER TO REMOVE

STOP USE AND ASK A DOCTOR IF RASH OR IRRITATION DEVELOPS OR LASTS

DIRECTIONS

- APPLY LIBERALLY 20 MINUTES BEFORE SUN EXPOSURE AND AS NEEDED
- FOR CHILDREN UNDER 6 MONTHS OF AGE, ASK A DOCTOR

SUN ALERT

LIMITING SUN EXPOSURE, WEARING PROTECTIVE CLOTHING AND USING SUNSCREEN REDUCES THE RISK OF AGING, SKIN CANCER AND OTHER HARMFUL EFFECTS OF THE SUN.

INGREDIENTS

WATER, ADIPIC ACID/ DIETHYLENE DIGLYCOL GLYCERIN CROSSPOLYMER, C 12-15 ALKYL BENZOATE, ALOE BARBADENSIS LEAF EXTRACT, RETINYL PALMITATE, TOCOPHERYL ACETATE SODIUM ASCORBYL PHOSPHATE, STEARETH-21, TRIETHANOLAMINE, PROPYLENE GLYCOL, DECYL GLUCOSIDE, SORBITAN STEARATE, STEARETH-2, ACRYLATES/ C 10-30 ALKYL ACETATE CROSSPOLYMER, DIAZOLIDINYL UREA, METHYLPARABEN, CARBOMER, HYDROXYPROPYL, METHYLCELLULOSE, DISODIUM EDTA, PROPYLPARABEN

IMAGE OF LABEL

SPF30LotionLabel.jpg